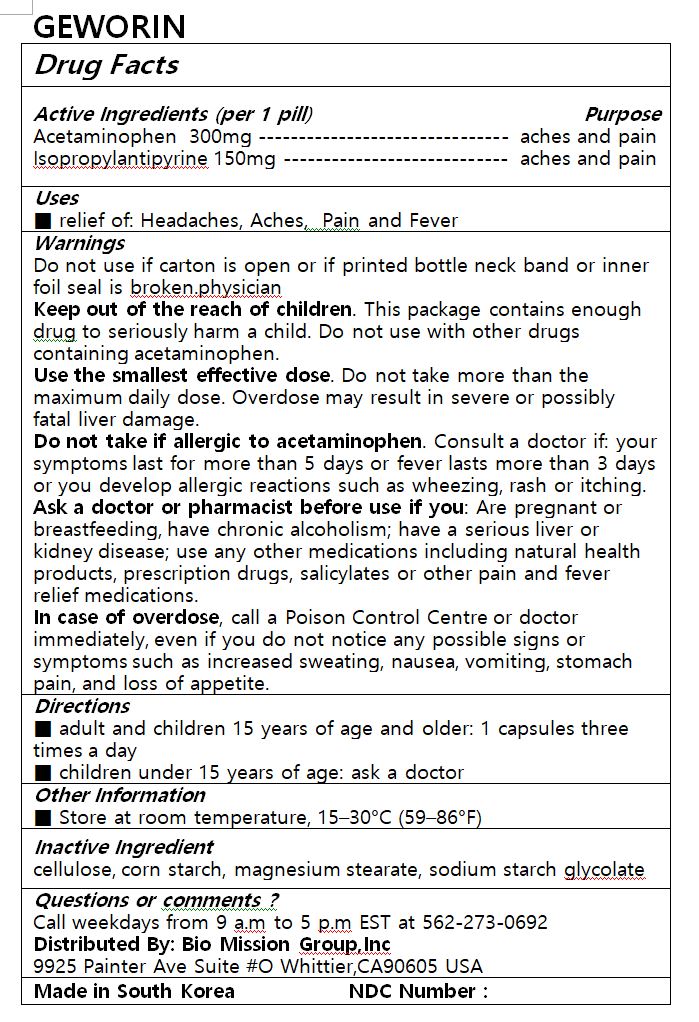 DRUG LABEL: GEWORIN
NDC: 72988-0036 | Form: TABLET
Manufacturer: Lydia Co., Ltd.
Category: otc | Type: HUMAN OTC DRUG LABEL
Date: 20230809

ACTIVE INGREDIENTS: ACETAMINOPHEN 300 mg/1 1; PROPYPHENAZONE 150 mg/1 1
INACTIVE INGREDIENTS: MAGNESIUM STEARATE

ACTIVE INGREDIENT

Acetaminophen, Isopropylantipyrine

PURPOSE

relief of: Headaches, Aches, Pain and Fever

Keep out of reach of children

INDICATIONS AND USAGE

■ adult and children 15 years of age and older: 1 capsules three times a day

■ children under 15 years of age: ask a doctor

Warnings

Do not use if carton is open or if printed bottle neck band or inner foil seal is broken.physician

Keep out of the reach of children. This package contains enough drug to seriously harm a child. Do not use with other drugs containing acetaminophen.

Use the smallest effective dose. Do not take more than the maximum daily dose. Overdose may result in severe or possibly fatal liver damage.

Do not take if allergic to acetaminophen. Consult a doctor if: your symptoms last for more than 5 days or fever lasts more than 3 days or you develop allergic reactions such as wheezing, rash or itching.

Ask a doctor or pharmacist before use if you: Are pregnant or breastfeeding, have chronic alcoholism; have a serious liver or kidney disease; use any other medications including natural health products, prescription drugs, salicylates or other pain and fever relief medications.

In case of overdose, call a Poison Control Centre or doctor immediately, even if you do not notice any possible signs or symptoms such as increased sweating, nausea, vomiting, stomach pain, and loss of appetite.

INACTIVE INGREDIENT

cellulose, corn starch, magnesium stearate, sodium starch glycolate

DOSAGE AND ADMINISTRATION

for oral use